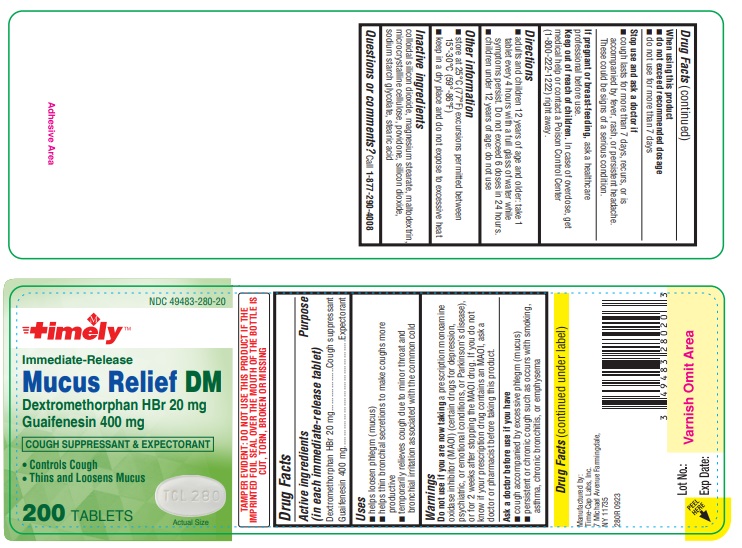 DRUG LABEL: MUCOSA DM
NDC: 49483-280 | Form: TABLET
Manufacturer: TIME CAP LABORATORIES, INC.
Category: otc | Type: HUMAN OTC DRUG LABEL
Date: 20250208

ACTIVE INGREDIENTS: GUAIFENESIN 400 mg/1 1; DEXTROMETHORPHAN HYDROBROMIDE 20 mg/1 1
INACTIVE INGREDIENTS: SILICON DIOXIDE; MAGNESIUM STEARATE; MALTODEXTRIN; CELLULOSE, MICROCRYSTALLINE; POVIDONE; SODIUM STARCH GLYCOLATE TYPE A POTATO; STEARIC ACID

280R Timely 49483-280 Dextromethorphan HBr 20 mg and Guaifenesin 400 mg Tablets

Active ingredients (in each immediate-release tablet)

Dextromethorphan HBr 20 mg

Guaifenesin 400 mg

Purpose

Cough suppressant

Expectorant

Uses
• helps loosen phlegm (mucus)
• helps thin bronchial secretions to make coughs more productive
• temporarily relieves cough due to minor throat and bronchial irritation associated with the common cold

Warnings

Do not use if you are now taking a prescription monoamine oxidase inhibitor (MAOI) (certain drugs for depression, psychiatric, or emotional conditions, or Parkinson's disease), or for 2 weeks after stopping the MAOI drug. If you do not know if your prescription drug contains an MAOI, ask a doctor or pharmacist before taking this product.

Ask a doctor before use if you have

- cough accompanied by excessive phlegm (mucus)
- persistent or chronic cough such as occurs with smoking, asthma, chronic bronchitis, or emphysema

When using this product

- do not exceed recommended dosage
- do not use for more than 7 days

Stop use and ask a doctor if

- cough lasts for more than 7 days, recurs, or is accompanied by fever, rash, or persistent headache. These could be signs of a serious condition.

PREGNANCY OR BREAST FEEDING

If pregnant or breast-feeding, ask a healthcare professional before use

Keep out of reach of children. In case of overdose, get medical help or contact a Poison Control Center (1-800-222-1222) right away.

Directions

- adults and children 12 years of age and older: take 1 tablet every 4 hours with a full glass of water while symptoms persist. Do not exceed 6 doses in 24 hours.
- children under 12 years of age: do not use

Other information

- store at 25°C (77°F) excursions permitted between 15°-30°C (59°-86°F)
- keep in a dry place and do not expose to excessive heat

INACTIVE INGREDIENT

Inactive ingredients colloidal silicon dioxide, magnesium stearate, maltodextrin, microcrystalline cellulose, povidone, silicon dioxide, sodium starch glycolate, stearic acid

Questions or comments?

Call 1-877-290-4008